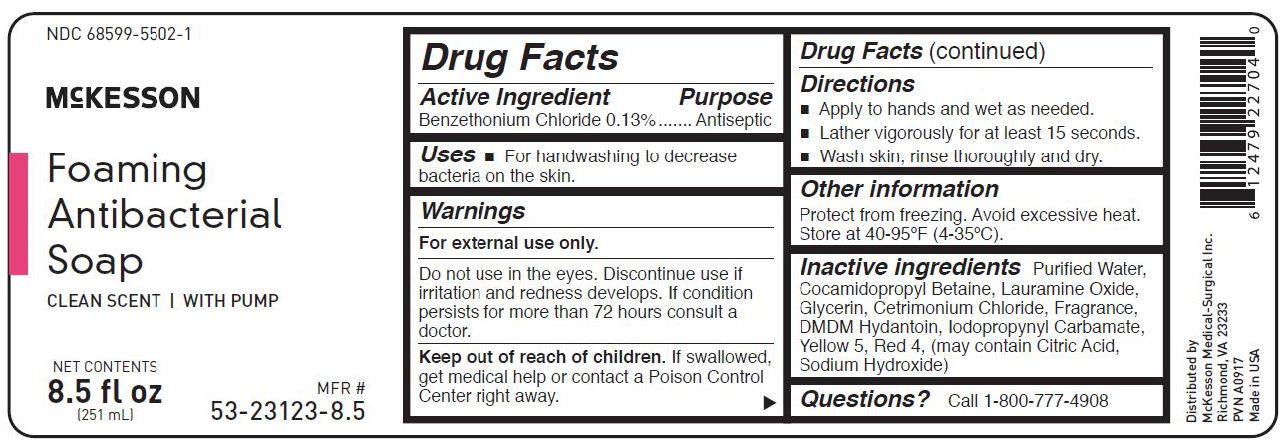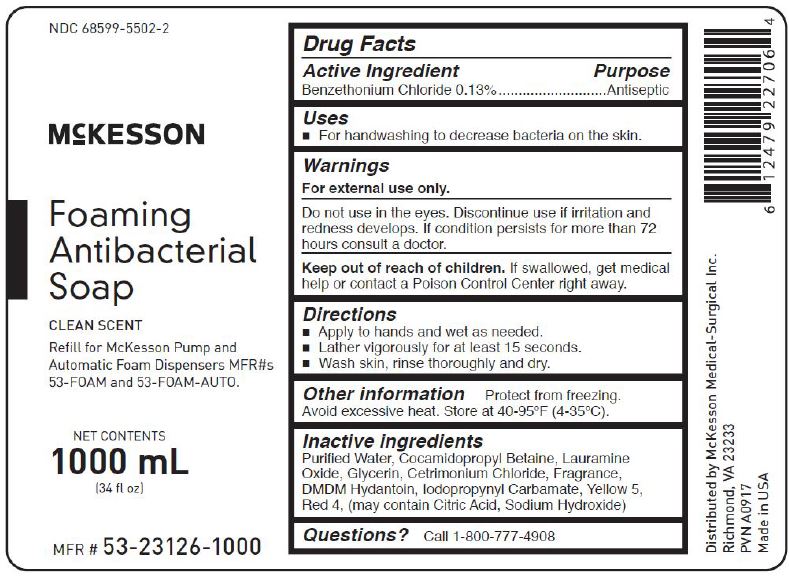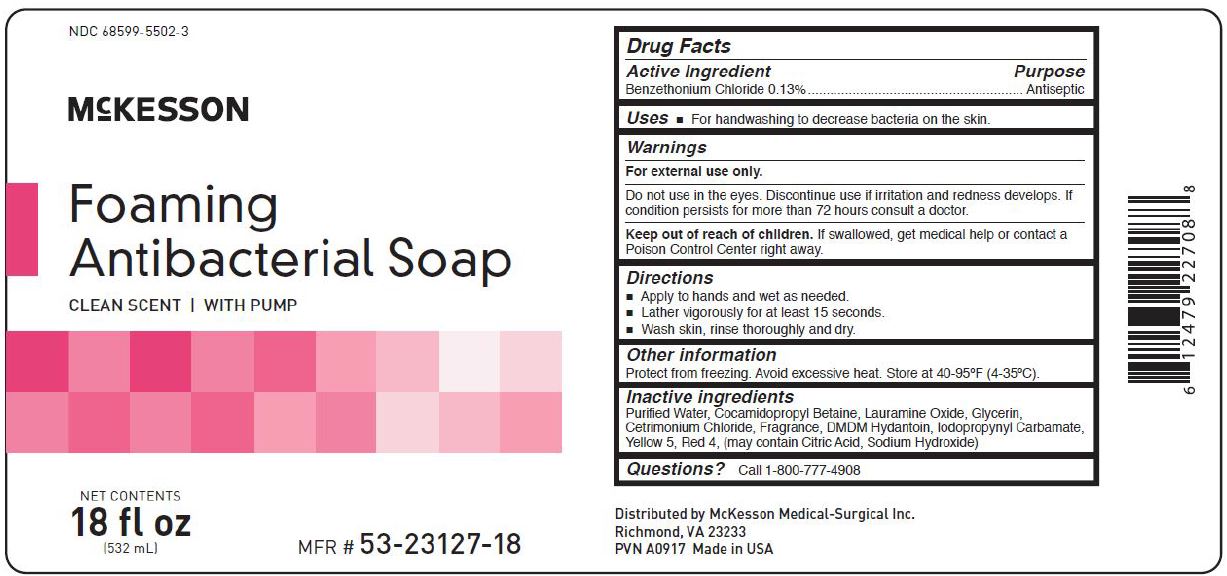 DRUG LABEL: Antibacterial
NDC: 68599-5502 | Form: LIQUID
Manufacturer: McKesson
Category: otc | Type: HUMAN OTC DRUG LABEL
Date: 20241011

ACTIVE INGREDIENTS: BENZETHONIUM CHLORIDE 0.13 g/100 mL
INACTIVE INGREDIENTS: LAURAMINE OXIDE; CETRIMONIUM CHLORIDE; DMDM HYDANTOIN; IODOPROPYNYL BUTYLCARBAMATE; WATER; COCAMIDOPROPYL BETAINE; GLYCERIN; FD&C RED NO. 4; FD&C YELLOW NO. 5

McKESSON FOAMING ANTIBACTERIAL SOAP

Drug Facts

Active Ingredient

Benzethonium Chloride @ 0.13%

PURPOSE

PurposeAntiseptic

Uses

For handwashing to decrease bacteria on the skin.

Warnings
For external use only.

Do not use in the eyes. Discontinue use if irritation and redness develops. If condition persists for more than 72 hours consult a doctor.

Keep out of reach of children.If swallowed, get medical help or
contact a Poison Control Center right away.

Directions
• Apply to hands and wet as needed.
• Lather vigorously for at least 15 seconds.
• Wash skin, rinse thoroughly and dry.

Other information- Protect from freezing. Avoid excessive heat.

Inactive Ingredients:
Purified Water, Cocamidopropyl Betaine, Lauramine Oxide, Glycerin, Cetrimonium Chloride, Fragrance, DMDM Hydantoin, Iodopropynyl Carbamate, Yellow 5, Red 4, (may contain Citric Acid, Sodium Hydroxide)

General Questions?Call 1-800-777-4908

PACKAGE LABEL

NDC 68599-5502-1
McKesson
Foaming Antibacterial Soap
Clean Scent with Pump
Net Contents
8.5 fl oz
(251 mL)

PACKAGE LABEL

NDC 68599-5502-2
McKesson
Foaming Antibacterial Soap
Clean Scent
Refill for McKesson Pump and Automatic Foam Dispensers MFR#s 53-FOAM and 53-Foam-Auto
Net Contents
1000 mL
(34 fl oz)

PACKAGE LABEL

NDC 68599-5502-3
McKesson
Foaming Antibacterial Soap
Clean Scent with Pump
Net Contents
18 fl oz
(532 mL)